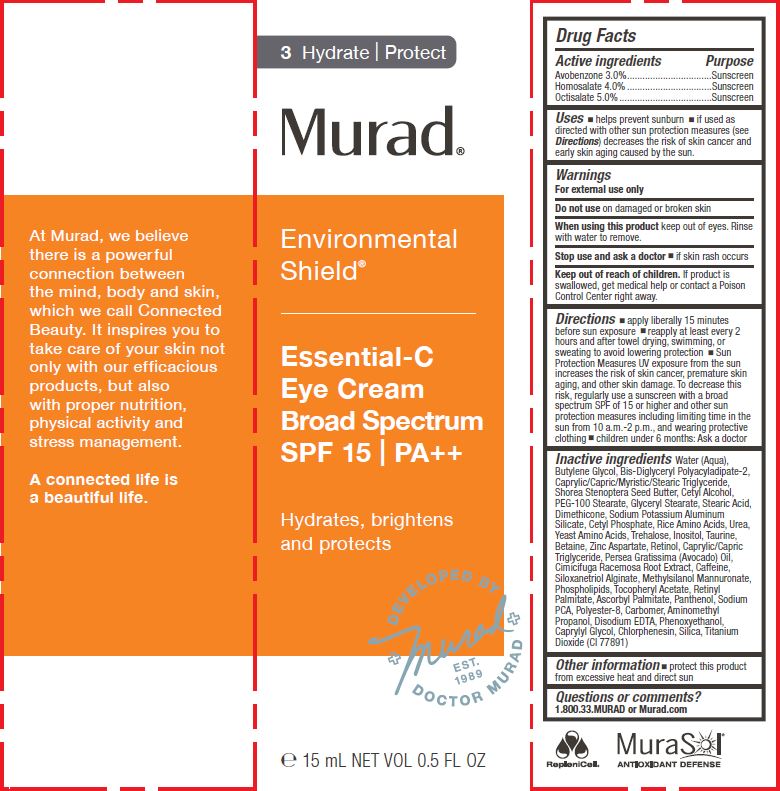 DRUG LABEL: MURAD - ENVIRONMENTAL SHIELD - ESSENTIAL-C EYE 
NDC: 70381-109 | Form: CREAM
Manufacturer: Murad, LLC
Category: otc | Type: HUMAN OTC DRUG LABEL
Date: 20210129

ACTIVE INGREDIENTS: AVOBENZONE 3 g/100 mL; HOMOSALATE 4 g/100 mL; OCTISALATE 5 g/100 mL
INACTIVE INGREDIENTS: WATER; BUTYLENE GLYCOL; BIS-DIGLYCERYL POLYACYLADIPATE-2; MEDIUM-CHAIN TRIGLYCERIDES; SHOREA STENOPTERA SEED BUTTER; CETYL ALCOHOL; PEG-100 STEARATE; GLYCERYL MONOSTEARATE; STEARIC ACID; DIMETHICONE; PERLITE; CETYL PHOSPHATE; RICE GERM; UREA; AMINO ACIDS, SOURCE UNSPECIFIED; TREHALOSE; INOSITOL; TAURINE; BETAINE; ZINC ASPARTATE; RETINOL; AVOCADO OIL; BLACK COHOSH; CAFFEINE; SILANETRIOL; ACEFYLLINE METHYLSILANOL MANNURONATE; OMEGA-3 FATTY ACIDS; .ALPHA.-TOCOPHEROL ACETATE; VITAMIN A PALMITATE; ASCORBYL PALMITATE; PANTHENOL; SODIUM PYRROLIDONE CARBOXYLATE; POLYESTER-8 (1400 MW, CYANODIPHENYLPROPENOYL CAPPED); CARBOMER HOMOPOLYMER, UNSPECIFIED TYPE; AMINOMETHYLPROPANOL; EDETATE DISODIUM; PHENOXYETHANOL; CAPRYLYL GLYCOL; CHLORPHENESIN; SILICON DIOXIDE; TITANIUM DIOXIDE

MURAD - ENVIRONMENTAL SHIELD - ESSENTIAL-C EYE CREAM SPF 15

ACTIVE INGREDIENTS

Avobenzone 3.0%
Homosalate 4.0%
Octisalate 5.0%

PURPOSE

SUNSCREEN

USES

- helps prevent sunburn
- if used as directed with other sun protection measures (see Directions) decreases the risk of skin cancer and early skin aging caused by the sun.

WARNINGS

For external use only
Do not use on damaged or broken skin
When using this product keep out of eyes. Rinse with water to remove.
Stop use and ask a doctor

- if rash occurs

Keep out of reach of children. If product is swallowed, get medical help or contact a Poison Control Center right away.

DIRECTIONS

- apply liberally 15 minutes before sun exposure
- use a water resistant sunscreen if swimming or sweating
- reapply at least every 2 hours
- Sun Protection Measures.pending time in the sun increases your risk of skin cancer and early skin aging. To decrease this risk, regularly use a sunscreen with a Broad Spectrum SPF value of 15 or higher and other sun protection measures including:
- limit time in the sun, especially from 10 a.m. - 2 p.m.
- wear long-sleeved shirts, pants, hats, and sunglasses.
- children under 6 months of age: ask a doctor

INACTIVE INGREDIENTS

Water (Aqua), Butylene Glycol, Bis-Diglyceryl Polyacyladipate-2, Caprylic/Capric/Myristic/Stearic Triglyceride, Shorea Stenoptera Seed Butter, Cetyl Alcohol, PEG-100 Stearate, Glyceryl Stearate, Stearic Acid, Dimethicone, Sodium Potassium Aluminum Silicate, Cetyl Phosphate, Rice Amino Acids, Urea, Yeast Amino Acids, Trehalose, Inositol, Taurine, Betaine, Zinc Aspartate, Retinol, Caprylic/Capric Triglyceride, Persea Gratissima (Avocado) Oil, Cimicifuga Racemosa Root Extract, Caffeine, Siloxanetriol Alginate, Methylsilanol Mannuronate, Phospholipids, Tocopheryl Acetate, Retinyl Palmitate, Ascorbyl Palmitate, Panthenol, Sodium PCA, Polyester-8, Carbomer, Aminomethyl Propanol, Disodium EDT , Phenoxyethanol,
Caprylyl Glycol, Chlorphenesin, Silica, Titanium Dioxide (CI 77891)

OTHER INFORMATION

- protect this product from excessive heat and direct sun

QUESTIONS OR COMMENTS?

1.800.33.MURAD or Murad.com